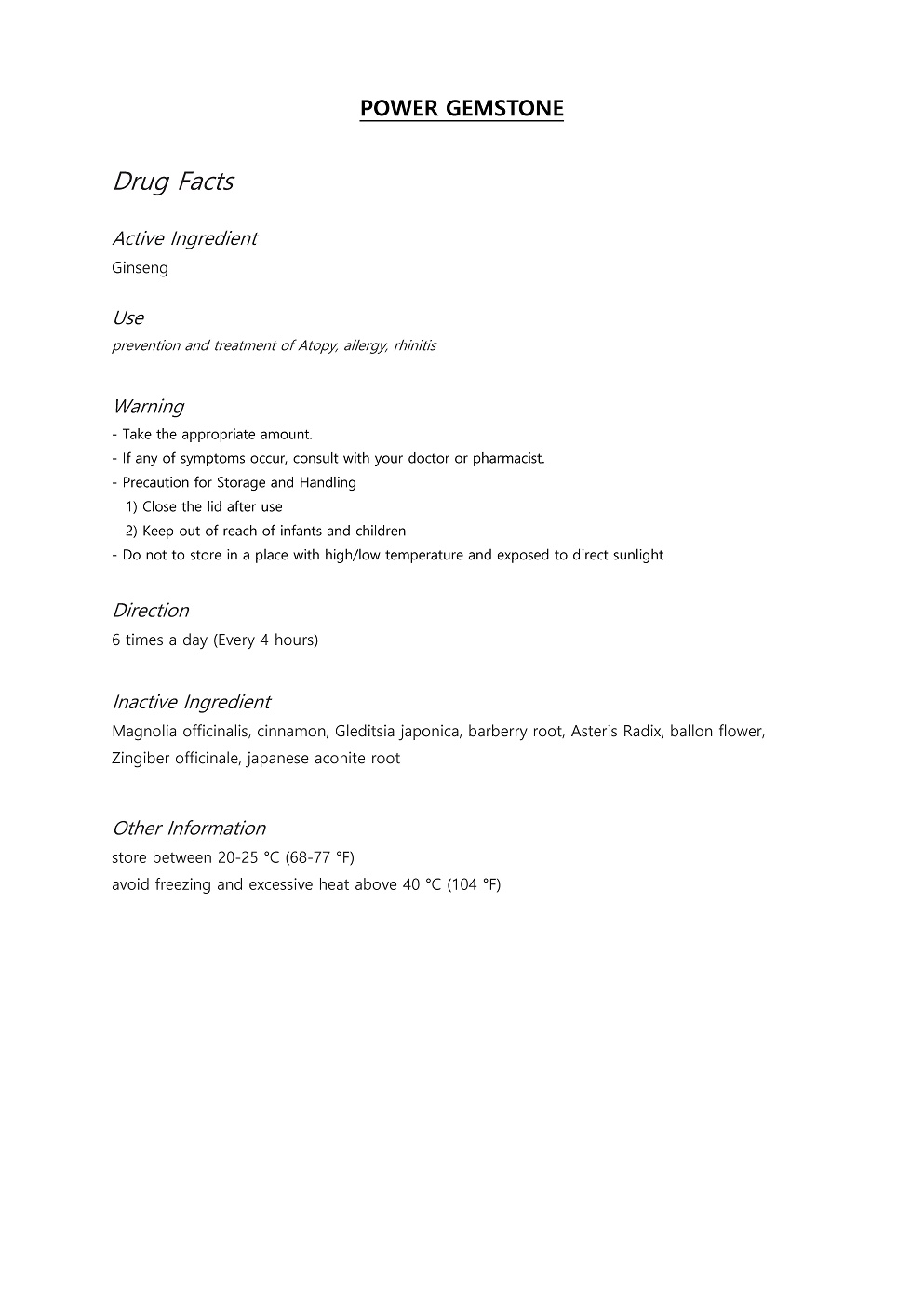 DRUG LABEL: POWER GEMSTONE
NDC: 71960-0003 | Form: PILL
Manufacturer: Myeong SA
Category: otc | Type: HUMAN OTC DRUG LABEL
Date: 20200116

ACTIVE INGREDIENTS: PANAX GINSENG WHOLE 20 g/100 g
INACTIVE INGREDIENTS: MAGNOLIA OFFICINALIS WHOLE

ACTIVE INGREDIENT

ginseng

INACTIVE INGREDIENT

Magnolia officinalis, cinnamon, Gleditsia japonica, barberry root, Asteris Radix, ballon flower, Zingiber officinale, japanese aconite root

PURPOSE

prevention and treatment of Atopy, allergy, rhinitis

keep out or reach of the children

INDICATIONS AND USAGE

6 times a day (Every 4 hours)
Dose: 4g

WARNINGS

Take the appropriate amount.

If any of symptoms occur, consult with your doctor or pharmacist.

DOSAGE AND ADMINISTRATION

6 times a day